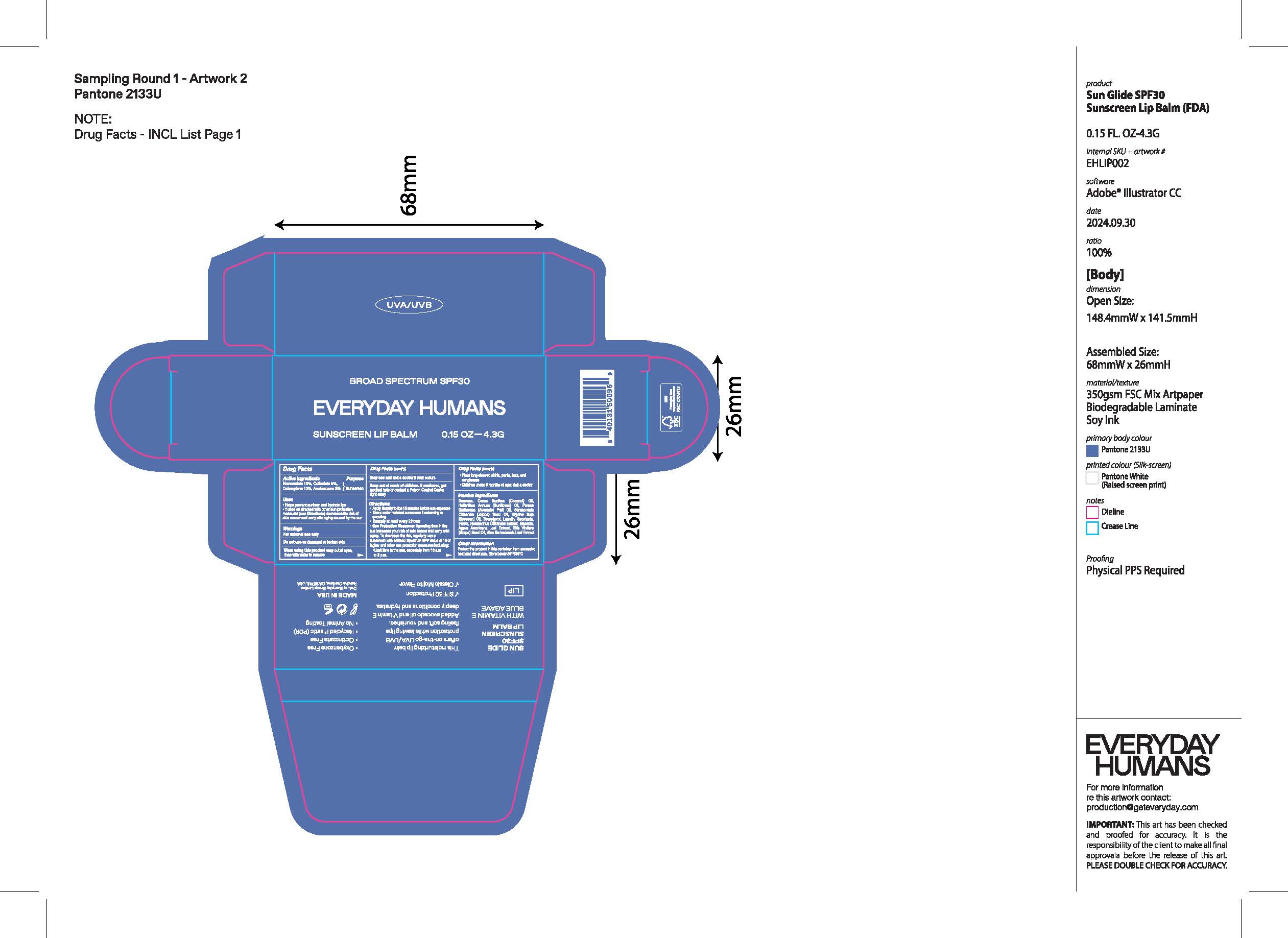 DRUG LABEL: Everyday Humans Sunscreen Lip Balm Broad Spectrum SPF30
NDC: 72098-010 | Form: OINTMENT
Manufacturer: Everyday Group Limted
Category: otc | Type: HUMAN OTC DRUG LABEL
Date: 20251204

ACTIVE INGREDIENTS: AVOBENZONE 3 mg/100 mg; HOMOSALATE 10 mg/100 mg; OCTISALATE 5 mg/100 mg; OCTOCRYLENE 10 mg/100 mg
INACTIVE INGREDIENTS: BEESWAX; COCOS NUCIFERA (COCONUT) OIL; HELIANTHUS ANNUUS (SUNFLOWER) SEED OIL; PERSEA GRATISSIMA (AVOCADO) OIL; SIMMONDSIA CHINENSIS (JOJOBA) SEED OIL; GLYCINE SOJA (SOYBEAN) SEED; TOCOPHEROL; LANOLIN; SACCHARIN; ROSMARINUS OFFICINALIS FLOWER; GLYCERIN; AGAVE AMERICANA LEAF; VITIS VINIFERA SEED; ALOE BARBADENSIS LEAF

Resting Beach Face SPF30 Anti-Pollution Sunscreen Serum

Active ingredients

Butyl Methoxydibenzoylmethane 3%

Homosalate 8%

Octyl Salicylate 4%

Octocrylene 2%

Purpose

Sunscreen

Uses

• Helps prevent sunburn and hydrate lips • If used as directed with other sun protection measures (see) decreases the risk of skin cancer and early skin aging caused by the sun

Warnings

For external use only

Do not use

on damaged or broken skin

When using this product

keep out of eyes, rinse with water to remove

Stop use and ask a doctor

if rash occurs

Keep out of reach of children.

If swallowed, get medical help or contact a Poison Control Center right away

Directions

• Apply liberally to lips 15 minutes before sun exposure • Use a water resistant sunscreen if swimming or sweating • Reapply at least every 2 hours • Spending time in the sun increases your risk of skin cancer and early skin aging. To decrease the risk, regularly use a sunscreen with a Broad Spectrum SPF value of 15 or higher and other sun protection measures including: • Limit time in the sun, especially from 10 a.m to 2 p.m. • Wear long-sleeved shirts, pants, hats, and sunglasses • Children under 6 months of age: Ask a doctor
Sun Protection Measures:

Inactive ingredients

Beeswax, Cocos Nucifera (Coconut) Oil, Helianthus Annuus (Sunflower) Oil, Persea Gratissima (Avocado) Fruit Oil, Simmondsia Chinensis (Jojoba) Seed Oil, Glycine Soja (Soybean) Oil, Tocopherol, Lanolin, Saccharin, Flavor, Rosmarinus Officinalis Extract, Glycerin, Agave Americana Leaf Extract, Vitis Vinifera (Grape) Seed Oil, Aloe Barbadensis Leaf Extract.

Other Information

Protect the product in this container from excessive heat and direct sun. Store below 86°F/30°C